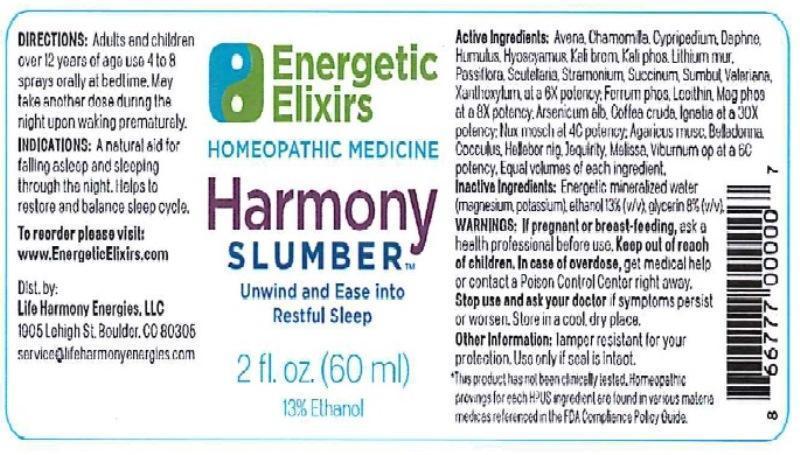 DRUG LABEL: Harmony Slumber
NDC: 69631-0001 | Form: LIQUID
Manufacturer: Life Harmony Energies, LLC.
Category: homeopathic | Type: HUMAN OTC DRUG LABEL
Date: 20160304

ACTIVE INGREDIENTS: AVENA SATIVA FLOWERING TOP 6 [hp_X]/60 mL; MATRICARIA RECUTITA 6 [hp_X]/60 mL; CYPRIPEDIUM PARVIFOLUM ROOT 6 [hp_X]/60 mL; DAPHNE ODORA BARK 6 [hp_X]/60 mL; HOPS 6 [hp_X]/60 mL; HYOSCYAMUS NIGER 6 [hp_X]/60 mL; POTASSIUM BROMIDE 6 [hp_X]/60 mL; POTASSIUM PHOSPHATE, DIBASIC 6 [hp_X]/60 mL; LITHIUM CHLORIDE 6 [hp_X]/60 mL; PASSIFLORA INCARNATA FLOWERING TOP 6 [hp_X]/60 mL; SCUTELLARIA LATERIFLORA 6 [hp_X]/60 mL; DATURA STRAMONIUM 6 [hp_X]/60 mL; AMBER 6 [hp_X]/60 mL; FERULA SUMBUL ROOT 6 [hp_X]/60 mL; VALERIAN 6 [hp_X]/60 mL; ZANTHOXYLUM AMERICANUM BARK 6 [hp_X]/60 mL; FERROSOFERRIC PHOSPHATE 8 [hp_X]/60 mL; EGG PHOSPHOLIPIDS 8 [hp_X]/60 mL; MANGANESE PHOSPHATE, DIBASIC 8 [hp_X]/60 mL; ARSENIC TRIOXIDE 30 [hp_X]/60 mL; ARABICA COFFEE BEAN 30 [hp_X]/60 mL; STRYCHNOS IGNATII SEED 30 [hp_X]/60 mL; NUTMEG 4 [hp_C]/60 mL; AMANITA MUSCARIA FRUITING BODY 6 [hp_C]/60 mL; ATROPA BELLADONNA 6 [hp_C]/60 mL; ANAMIRTA COCCULUS SEED 6 [hp_C]/60 mL; HELLEBORUS NIGER ROOT 6 [hp_C]/60 mL; ABRUS PRECATORIUS SEED 6 [hp_C]/60 mL; MELISSA OFFICINALIS 6 [hp_C]/60 mL; VIBURNUM OPULUS BARK 6 [hp_C]/60 mL
INACTIVE INGREDIENTS: WATER; MAGNESIUM; POTASSIUM; ALCOHOL; GLYCERIN

Harmony Slumber

Active Ingredient: Avena sativa, Chamomilla, Cypripedium pubescens, Daphne indica, Humulus lupulus, Hyoscyamus niger, Kali bromatum, Kali phosphoricum, Lithium muriaticum, Passiflora incarnata, Scutellaria lateriflora, Stramonium, Succinum, Sumbul, Valeriana officinalis, Xanthoxylum fraxineum at a 6X potency. Ferrum phosphoricum, Lecithin, Manganum phosphoricum at a 8X potency. Arsenicum album, Coffea cruda, Ignatia amara at a 30X potency. Nux moschata at 4C potency. Agaricus muscarius, Belladonna, Cocculus indicus, Helleborus niger, Jequirity, Melissa officinalis, Viburnum opulus at a 6C potency. Equal volumes of each ingredient.

Inactive Ingredient: Energetic mineralized water (magnesium, potassium). ethanol 13%(v/v). glycerin 8%(v/v).

WARNINGS

Warnings: If pregnant or breast-feeding, ask a health professional before use. Keep out of reach of children. In case of overdose, get medical help or contact a Poison Control Center right away. Stop use and ask your doctor if symptoms persist or worsen. Store in a cool, dry place.

Keep out of reach of children.

Other information: Tamper resistant for your protection. Use only if safety seal is intact.

*This product has not been clinically tested. Homeopathic provings for each HPUS ingredient are found in various materia medicas referenced in the FDA Compliance Policy Guide.

To reorder please visit: www.EnergeticElixirs.com

Dist. by:

Life Harmony Energies, LLC

1905 Lehigh St. Boulder, CO 80305

service@lifeharmonyenergies.com

PURPOSE

Indications: A natural aid for falling asleep and sleeping through the night. Helps to restore and balance sleep cycle.

DOSAGE AND ADMINISTRATION

Directions: Adults and children over 12 years of age use 4 to 8 sprays orally at bedtime. May take another dose during the night upon waking prematurely.

INDICATIONS AND USAGE

Indications: •A natural aid for falling asleep and sleeping through the night. •Helps to restore and balance sleep cycle.